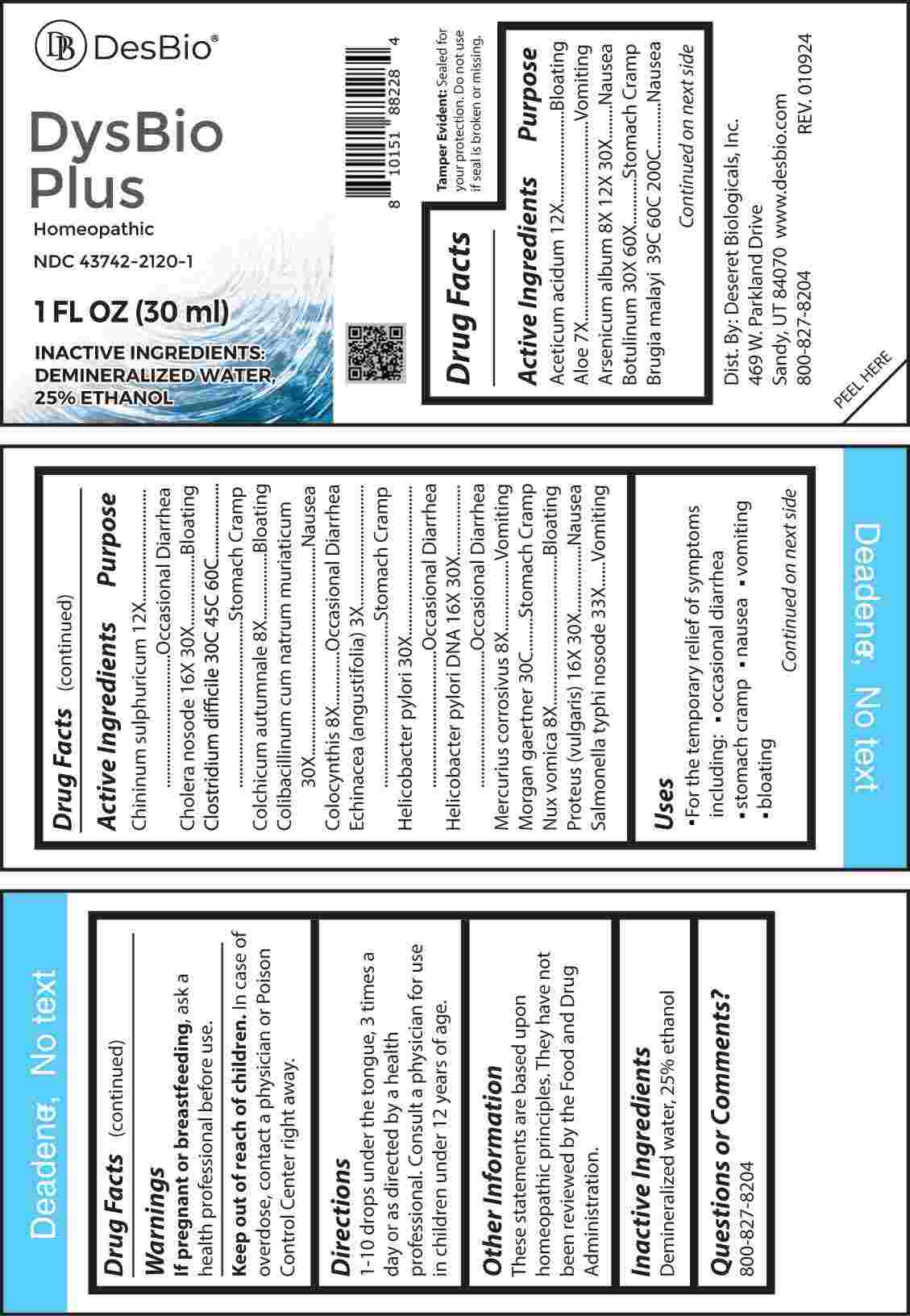 DRUG LABEL: Dysbio Plus
NDC: 43742-2120 | Form: LIQUID
Manufacturer: Deseret Biologicals, Inc.
Category: homeopathic | Type: HUMAN OTC DRUG LABEL
Date: 20240207

ACTIVE INGREDIENTS: ACETIC ACID 12 [hp_X]/1 mL; ALOE 7 [hp_X]/1 mL; ARSENIC TRIOXIDE 8 [hp_X]/1 mL; CLOSTRIDIUM BOTULINUM 30 [hp_X]/1 mL; BRUGIA MALAYI 39 [hp_C]/1 mL; QUININE SULFATE 12 [hp_X]/1 mL; VIBRIO CHOLERAE 16 [hp_X]/1 mL; CLOSTRIDIUM DIFFICILE 30 [hp_C]/1 mL; COLCHICUM AUTUMNALE BULB 8 [hp_X]/1 mL; ESCHERICHIA COLI 30 [hp_X]/1 mL; CITRULLUS COLOCYNTHIS FRUIT PULP 8 [hp_X]/1 mL; ECHINACEA ANGUSTIFOLIA WHOLE 3 [hp_X]/1 mL; HELICOBACTER PYLORI 30 [hp_X]/1 mL; HELICOBACTER PYLORI DNA 16 [hp_X]/1 mL; MERCURIC CHLORIDE 8 [hp_X]/1 mL; SALMONELLA ENTERICA ENTERICA SEROVAR ENTERITIDIS 30 [hp_C]/1 mL; STRYCHNOS NUX-VOMICA SEED 8 [hp_X]/1 mL; PROTEUS VULGARIS 16 [hp_X]/1 mL; SALMONELLA ENTERICA ENTERICA SEROVAR TYPHI 33 [hp_X]/1 mL
INACTIVE INGREDIENTS: WATER; ALCOHOL

DRUG FACTS:

ACTIVE INGREDIENTS:

Aceticum Acidum 12X, Aloe 7X, Arsenicum Album 8X, 12X, 30X, Botulinum 30X, 60X, Brugia Malayi 39C, 60C, 200C, Chininum Sulphuricum 12X, Cholera Nosode 16X, 30X, Clostridium Difficile 30C, 45C, 60C, Colchicum Autumnale 8X, Colibacillinum Cum Natrum Muriaticum 30X, Colocynthis 8X, Echinacea (Angustifolia) 3X, Helicobacter Pylori 30X, Helicobacter Pylori DNA 16X, 30X, Mercurius Corrosivus 8X, Morgan Gaertner 30C, Nux Vomica 8X, Proteus (Vulgaris) 16X, 30X, Salmonella Typhi Nosode 33X.

PURPOSE:

Aceticum Acidum - Bloating, Aloe - Vomiting, Arsenicum Album - Nausea, Botulinum – Stomach Cramp, Brugia Malayi - Nausea, Chininum Sulphuricum – Occasional Diarrhea, Cholera Nosode - Bloating, Clostridium Difficile – Stomach Cramp, Colchicum Autumnale - Bloating, Colibacillinum Cum Natrum Muriaticum - Nausea, Colocynthis – Occasional Diarrhea, Echinacea (Angustifolia) – Stomach Cramp, Helicobacter Pylori – Occasional Diarrhea, Helicobacter Pylori DNA – Occasional Diarrhea, Mercurius Corrosivus - Vomiting, Morgan Gaertner – Stomach Cramp, Nux Vomica - Bloating, Proteus (Vulgaris) - Nausea, Salmonella Typhi Nosode - Vomiting

USES:

• For the temporary relief of symptoms including:

• occasional diarrhea • stomach cramps

• nausea • vomiting • bloating

These statements are based upon homeopathic principles. They have not been reviewed by the Food and Drug Administration.

WARNINGS:

If pregnant or breast-feeding, ask a health professional before use.

Keep out of reach of children. In case of overdose, contact a physician or Poison Control Center right away.

Tamper Evident: Sealed for your protection. Do not use if seal is broken or missing.

KEEP OUT OF REACH OF CHILDREN:

In case of overdose, contact a physician or Poison Control Center right away.

DIRECTIONS:

1-10 drops under the tongue, 3 times a day or as directed by a health professional. Consult a physician for use in children under 12 years of age.

INACTIVE INGREDIENTS:

Demineralized water, 25% ethanol

QUESTIONS:

Dist. By: Deseret Biologicals, Inc.

469 W. Parkland Drive

Sandy, UT 84070 www.desbio.com

800-827-8204

PACKAGE LABEL DISPLAY:

DesBio

DysBio

Plus

Homeopathic

NDC 43742-2120-1

1 FL OZ (30 ml)